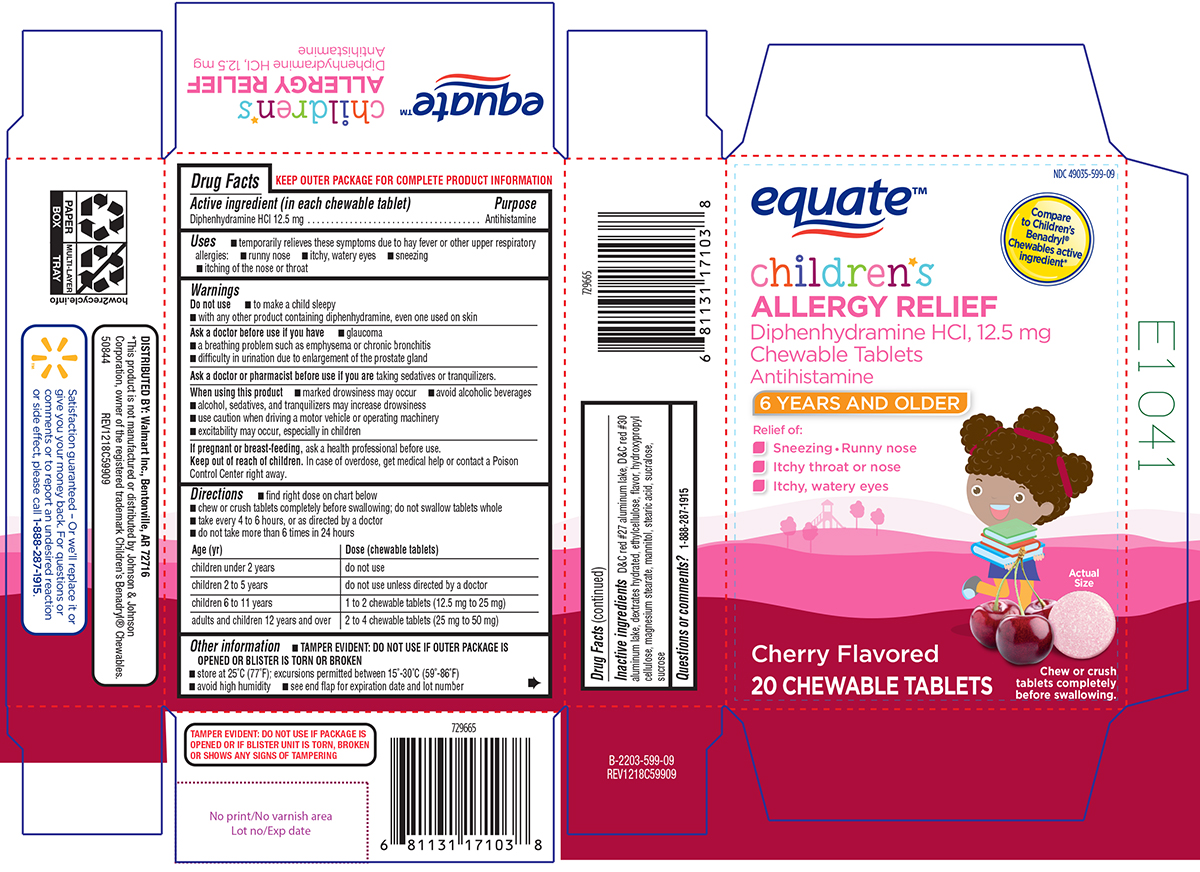 DRUG LABEL: Childrens Allergy Relief
NDC: 49035-599 | Form: TABLET, CHEWABLE
Manufacturer: Wal-Mart Stores Inc
Category: otc | Type: HUMAN OTC DRUG LABEL
Date: 20260127

ACTIVE INGREDIENTS: DIPHENHYDRAMINE HYDROCHLORIDE 12.5 mg/1 1
INACTIVE INGREDIENTS: D&C RED NO. 27 ALUMINUM LAKE; D&C RED NO. 30 ALUMINUM LAKE; DEXTROSE MONOHYDRATE; ETHYLCELLULOSE, UNSPECIFIED; HYDROXYPROPYL CELLULOSE, UNSPECIFIED; MAGNESIUM STEARATE; MANNITOL; STEARIC ACID; SUCRALOSE; SUCROSE

Equate 44-599

Active ingredient (in each chewable tablet)

Diphenhydramine HCl 12.5 mg

Purpose

Antihistamine

Uses

- temporarily relieves these symptoms due to hay fever or other upper respiratory allergies:
  - runny nose
  - itchy, watery eyes
  - sneezing
  - itching of the nose or throat

Warnings

Do not use

- to make a child sleepy
- with any other product containing diphenhydramine, even one used on skin

Ask a doctor before use if you have

- glaucoma
- a breathing problem such as emphysema or chronic bronchitis
- difficulty in urination due to enlargement of the prostate gland

Ask a doctor or pharmacist before use if you are

taking sedatives or tranquilizers.

When using this product

- marked drowsiness may occur
- avoid alcoholic beverages
- alcohol, sedatives, and tranquilizers may increase drowsiness
- use caution when driving a motor vehicle or operating machinery
- excitability may occur, especially in children

If pregnant or breast-feeding,

ask a health professional before use.

Keep out of reach of children.

In case of overdose, get medical help or contact a Poison Control Center right away.

Directions

- find right dose on chart below
- chew or crush tablets completely before swallowing; do not swallow tablets whole
- take every 4 to 6 hours, or as directed by a doctor
- do not take more than 6 times in 24 hours

Age (yr) | Dose (chewable tablets)
children under 2 years | do not use
children 2 to 5 years | do not use unless directed by a doctor
children 6 to 11 years | 1 to 2 chewable tablets (12.5 mg to 25 mg)
adults and children 12 years and over | 2 to 4 chewable tablets (25 mg to 50 mg)

Other information

- TAMPER EVIDENT: DO NOT USE IF OUTER PACKAGE IS OPENED OR BLISTER IS TORN OR BROKEN
- store at 25ºC (77ºF); excursions permitted between 15º-30ºC (59º-86ºF)
- avoid high humidity
- see end flap for expiration date and lot number

Inactive ingredients

D&C red #27 aluminum lake, D&C red #30 aluminum lake, dextrates hydrated, ethylcellulose, flavor, hydroxypropyl cellulose, magnesium stearate, mannitol, stearic acid, sucralose, sucrose

Questions or comments?

1-888-287-1915

Principal Display Panel

NDC 49035-599-09

equate™

Compare
to Children's
Benadryl®
Chewables active
ingredient*

children's
ALLERGY RELIEF
Diphenhydramine HCl, 12.5 mg
Chewable Tablets
Antihistamine

6 YEARS AND OLDER

Relief of:
• Sneezing • Runny nose
• Itchy throat or nose
• Itchy, watery eyes

Cherry Flavored

20 CHEWABLE TABLETS

Actual Size

Chew or crush tablets completely before swallowing.

TAMPER EVIDENT: DO NOT USE IF PACKAGE IS
OPENED OR IF BLISTER UNIT IS TORN, BROKEN
OR SHOWS ANY SIGNS OF TAMPERING

*This product is not manufactured or distributed by Johnson & Johnson
Corporation, owner of the registered trademark Children’s Benadryl® Chewables.
50844 REV1218C59909

DISTRIBUTED BY: Walmart Inc., Bentonville, AR 72716

Satisfaction guaranteed - Or we'll replace it or
give you your money back. For questions or
comments or to report an undesired reaction
or side effect, please call 1-888-287-1915.

Equate 44-599